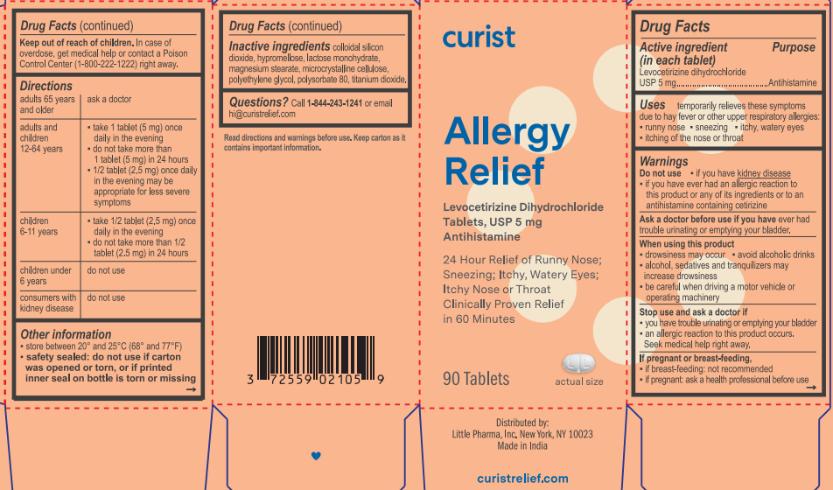 DRUG LABEL: Curist Allergy Relief
NDC: 72559-021 | Form: TABLET
Manufacturer: Little Pharma, Inc.
Category: otc | Type: HUMAN OTC DRUG LABEL
Date: 20250416

ACTIVE INGREDIENTS: LEVOCETIRIZINE DIHYDROCHLORIDE 5 mg/1 1
INACTIVE INGREDIENTS: TITANIUM DIOXIDE; HYPROMELLOSE 2910 (3 MPA.S); POLYETHYLENE GLYCOL 400; POLYSORBATE 80; LACTOSE MONOHYDRATE; MAGNESIUM STEARATE; MICROCRYSTALLINE CELLULOSE; HYPROMELLOSE 2910 (6 MPA.S); SILICON DIOXIDE

Curist Allergy Relief Tablet (levocetirizine 5 mg)

Drug Facts

Active ingredient (in each tablet)

Levocetirizine dihydrochloride USP 5 mg

Purpose

Antihistamine

Uses

temporarily relieves these symptoms due to hay fever or other respiratory allergies:

- runny nose
- sneezing
- itchy, watery eyes
- itching of the nose or throat

Warnings

Do not use

- if you have kidney disease
- if you have ever had an allergic reaction to this product or any of its ingredients or to an antihistamine containing cetirizine

Ask a doctor before use if you have ever had trouble urinating or emptying your bladder.

When using this product

- drowsiness may occur
- avoid alcoholic drinks
- alcohol, sedatives, and tranquilizers may increase drowsiness
- be careful when driving a motor vehicle or operating machinery

Stop use and ask a doctor if

- you have trouble urinating or emptying your bladder
- an allergic reaction to this product occurs. Seek medical help right away.

If pregnant or breast-feeding,

- if breast-feeding: not recommended
- if pregnant: ask a health professional before use

Keep out of reach of children. In case of overdose, get medical help or contact a Poison Control Center (1-800-222-1222) right away.

Directions

adults 65 years and older | ask a doctor
adults and children 12-64 years | - take 1 tablet (5 mg) once daily in the evening - do not take more than 1 tablet (5 mg) in 24 hours - ½ tablet (2.5 mg) once daily in the evening may be appropriate for less severe symptoms
children 6-11 years | - take ½ tablet (2.5 mg) once daily in the evening - do not take more than ½ tablet (2.5 mg) in 24 hours
children under 6 years | do not use
consumers with kidney disease | do not use

Other information

- store between 20° and 25°C (68° and 77°F)
- safety sealed: do not use if carton was opened or torn, or if printed inner seal on bottle is torn or missing

Inactive ingredients

colloidal silicon dioxide, hypromellose, lactose monohydrate, magnesium stearate, microcrystalline cellulose, polyethylene glycol, polysorbate 80, titanium dioxide.

Questions?

Call 1-844-243-1241 or email hi@curistrelief.com

Read directions and warnings before use. Keep carton as it contains important information.

Distributed by:

Little Pharma, Inc. New York, NY 10023

Made in India

curistrelief.com

PACKAGE LABEL

curist

Allergy Relief

Levocetirizine Dihydrochloride Tablets, USP 5 mg

Antihistamine

24 Hour Relief of Runny Nose; Sneezing; Itchy, Watery Eyes; Itchy Nose or Throat

Clinically Proven Relief in 60 Minutes

90 Tablets

actual size